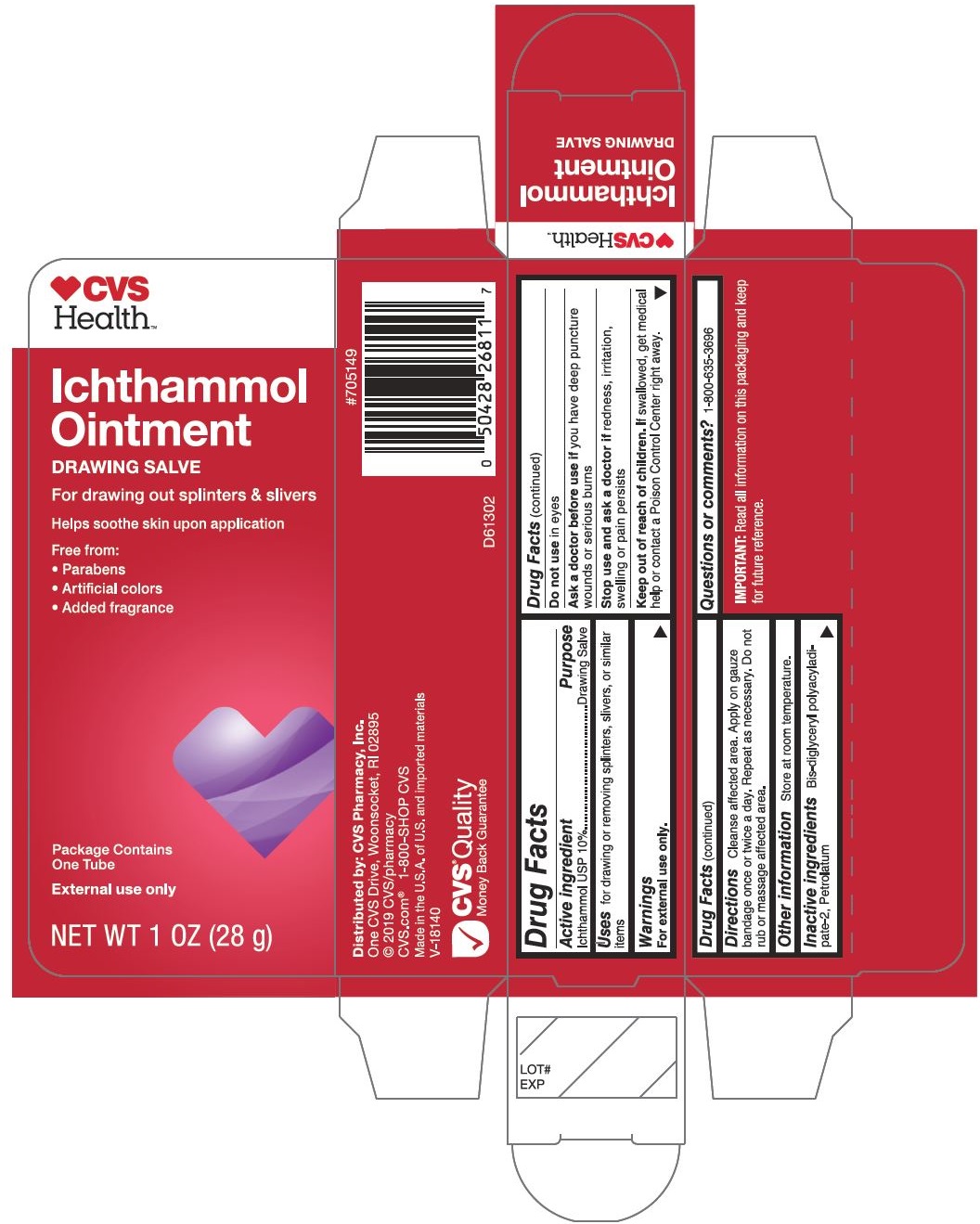 DRUG LABEL: CVS IchthammolOintment Salve
NDC: 69842-790 | Form: OINTMENT
Manufacturer: CVS Health
Category: otc | Type: HUMAN OTC DRUG LABEL
Date: 20220113

ACTIVE INGREDIENTS: ICHTHAMMOL 100 mg/1 g
INACTIVE INGREDIENTS: BIS-DIGLYCERYL POLYACYLADIPATE-2; PETROLATUM

CVS lchthammol Ointment Drawing Salve

PURPOSE

Drawing Salve

Drug Facts

Active ingredient | Purpose
lchthammol USP 10% | Drawing Salve

Uses

for drawing or removing splinters, slivers, or similar items

Warnings

For external use only.

Drug Facts (continued)

Do not use in eyes

Ask a doctor before use if you have deep puncture wounds or serious burns

Stop use and ask doctor if redness, irritation, swelling or pain persists

Keep out of reach of children. If swallowed, get medical help or contact a Poison Control Center right away.

Drug Facts (continued)

Directions

Cleanse affected area. Apply on gauze bandage once or twice a day. Repeat as necessary. Do not rub or massage affected area.

Other information

Store at room temperature.

Inactive ingredients

Bis-diglyceryl polyacyladipate-2, Petrolatum

Questions or comments?

1-800-635-3696